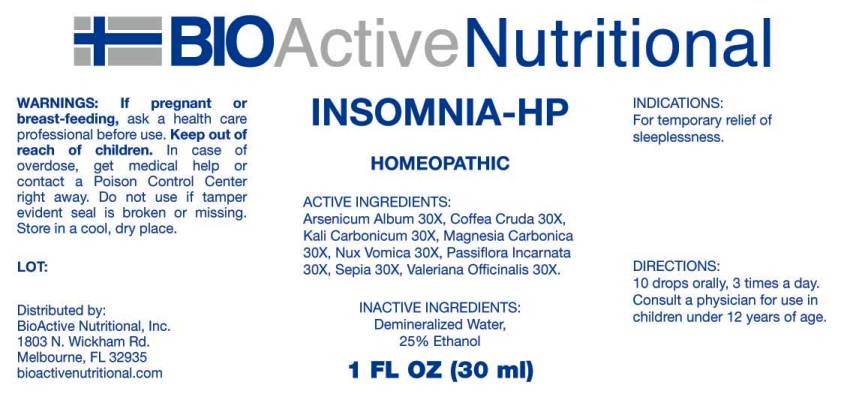 DRUG LABEL: Insomnia
NDC: 43857-0142 | Form: LIQUID
Manufacturer: BioActive Nutritional, Inc.
Category: homeopathic | Type: HUMAN OTC DRUG LABEL
Date: 20161220

ACTIVE INGREDIENTS: ARSENIC TRIOXIDE 30 [hp_X]/1 mL; ARABICA COFFEE BEAN 30 [hp_X]/1 mL; POTASSIUM CARBONATE 30 [hp_X]/1 mL; MAGNESIUM CARBONATE 30 [hp_X]/1 mL; STRYCHNOS NUX-VOMICA SEED 30 [hp_X]/1 mL; PASSIFLORA INCARNATA FLOWERING TOP 30 [hp_X]/1 mL; SEPIA OFFICINALIS JUICE 30 [hp_X]/1 mL; VALERIAN 30 [hp_X]/1 mL
INACTIVE INGREDIENTS: WATER; ALCOHOL

Drug Facts:

ACTIVE INGREDIENTS:

Arsenicum Album 30X, Coffea Cruda 30X, Kali Carbonicum 30X, Magnesia Carbonica 30X, Nux Vomica 30X, Passiflora Incarnata 30X, Sepia 30X, Valeriana Officinalis 30X.

INDICATIONS:

For temporary relief of sleeplessness.

WARNINGS:

If pregnant or breast-feeding, ask a health care professional before use.

Keep out of reach of children. In case of overdose, get medical help or contact a Poison Control Center right away.

Do not use if tamper evident seal is broken or missing.

Store in cool, dry place.

DIRECTIONS:

10 drops orally, 3 times a day. Consult a physician for use in children under 12 years of age.

INACTIVE INGREDIENTS:

Demineralized Water, 25% Ethanol.

Keep out of reach of children. In case of overdose, get medical help or contact a Poison Control Center right away.

INDICATIONS:

For temporary relief of sleeplessness.

QUESTIONS:

Distributed by:
BioActive Nutritional, Inc.
1803 N. Wickham Rd.
Melbourne, FL 32935
bioactivenutritional.com

PACKAGE LABEL DISPLAY:

BIOActive Nutritional

INSOMNIA HP

HOMEOPATHIC

1 FL OZ (30 ml)